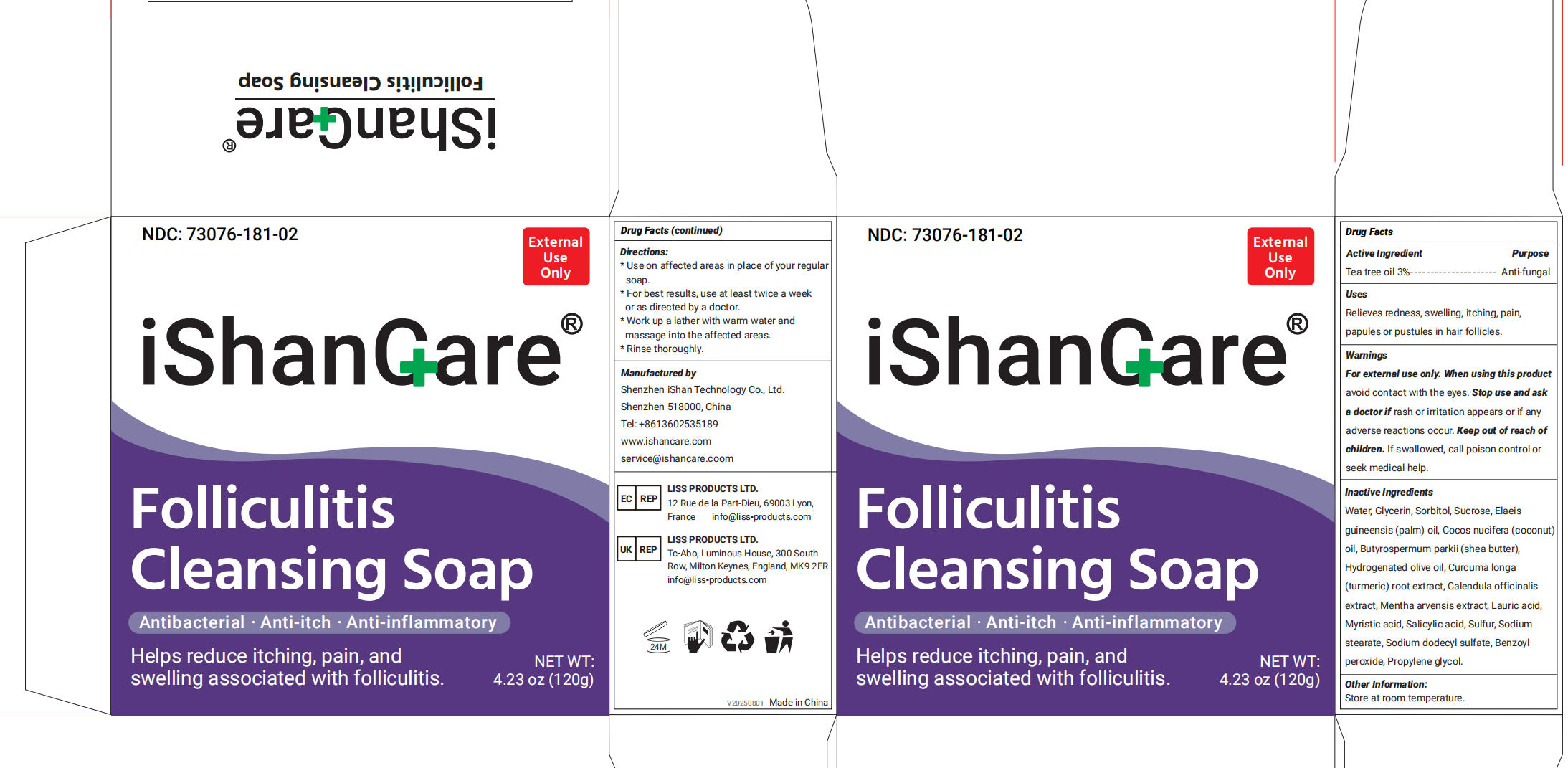 DRUG LABEL: iShanCare Folliculitis Cleansing
NDC: 73076-181 | Form: SOAP
Manufacturer: Shenzhen Ishan Technology Co., Ltd
Category: otc | Type: HUMAN OTC DRUG LABEL
Date: 20260212

ACTIVE INGREDIENTS: TEA TREE OIL 3 g/100 g
INACTIVE INGREDIENTS: SORBITOL; MENTHA ARVENSIS WHOLE; COCOS NUCIFERA (COCONUT) OIL; ELAEIS GUINEENSIS (PALM) OIL; WATER; CALENDULA OFFICINALIS WHOLE; CHRYSANTHELLUM INDICUM WHOLE; WOLFIPORIA COCOS WHOLE; HYDROGENATED OLIVE OIL; BUTYROSPERMUM PARKII (SHEA) BUTTER; GLYCERIN; BEESWAX; SUCROSE; MYRISTIC ACID; SODIUM DODECYLBENZENESULFONATE; LAURIC ACID; SODIUM STEARATE; CURCUMA LONGA (TURMERIC) ROOT OIL

Active ingredients

Tea tree oil 3% ------------------------------- Anti-fungal

Inactive Ingredients

Water, Glycerin, Sorbitol, Sucrose, Elaeisguineensis (palm) oil, Cocos nucifera (coconutoil, Butyrospermum parkii (shea butter),
Hydrogenated olive oil, Curcuma longa(turmeric) root extract, Calendula officinalisextract, Mentha arvensis extract, Lauric acid,Myristic acid, Salicylic acid, Sulfur, Sodiumstearate, Sodium dodecyl sulfate, Benzoylperoxide, Propylene glycol.

Uses

Helps relieve dryness, itching, redness,
and discomfort caused by eczema-prone skin.

Warnings

For external use only

When using this product

avoid contact with the eyes

Stop use

Stop use and ask a doctor if rash or irritation appears or if any
adverse reactions occur

Ask a doctor

Stop use and ask
a doctor if rash or irritation appears or if any
adverse reactions occur

Keep out of reach of children

If swallowed, call a poison control center or seek medical attention immediately.

Dosage and administration

First, wet your skin. Then lather the soap in
your hands, and apply the lather to your face
or body in a circular motion. Leave on skin for
two minutes, then rinse completely and pat dry
gently.

Other information

Store at room temperature.

INDICATIONS AND USAGE

First, wet your skin. Then lather the soap in your hands, and apply the lather to your face or body in a circular motion. Leave on skin fortwo minutes, then rinse completely and pat dry gently.